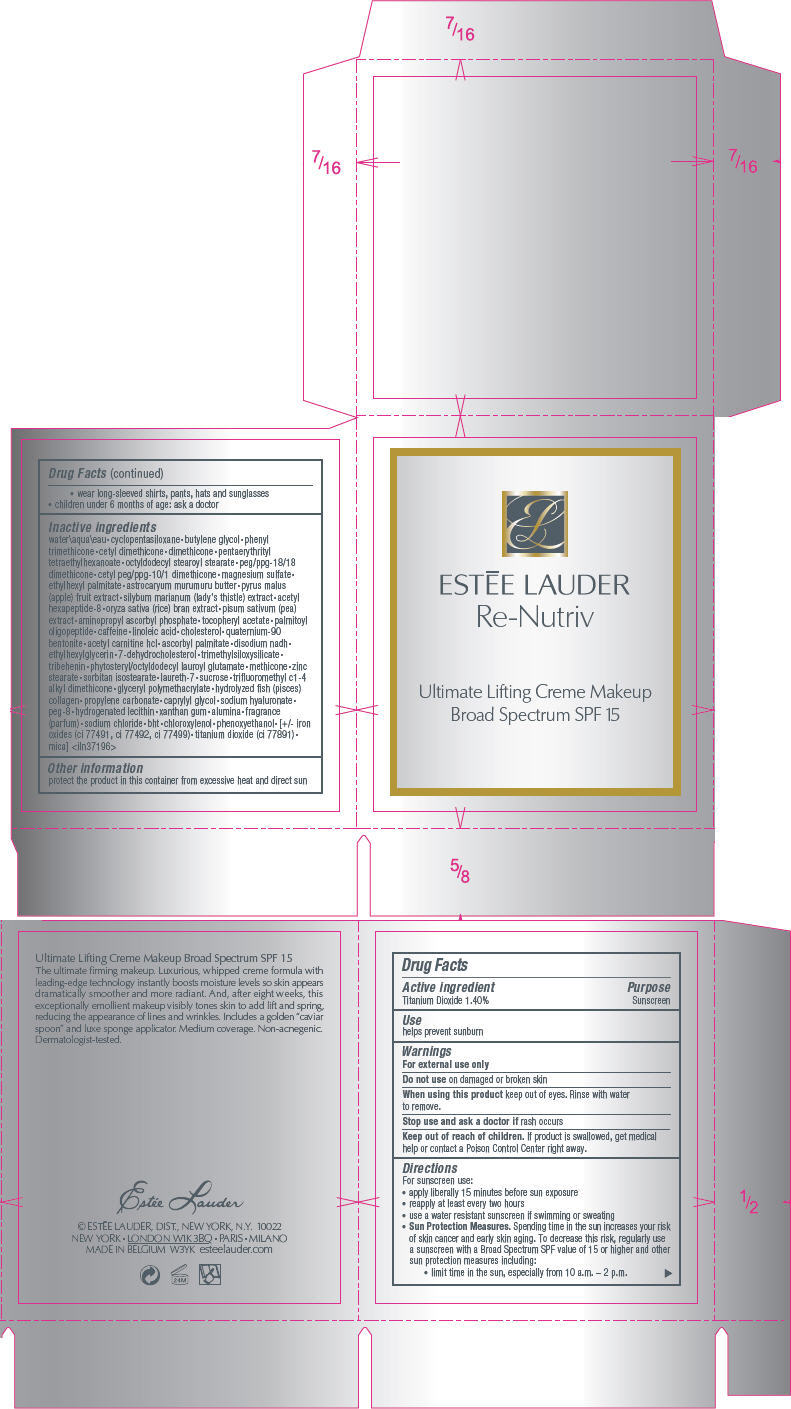 DRUG LABEL: RE-NUTRIV 
NDC: 11559-724 | Form: CREAM
Manufacturer: ESTEE LAUDER INC
Category: otc | Type: HUMAN OTC DRUG LABEL
Date: 20120627

ACTIVE INGREDIENTS: TITANIUM DIOXIDE 1.4 mL/100 mL
INACTIVE INGREDIENTS: water; cyclomethicone 5; butylene glycol; phenyl trimethicone; dimethicone; pentaerythrityl tetraethylhexanoate; octyldodecyl stearoyl stearate; peg/ppg-18/18 dimethicone; magnesium sulfate; ethylhexyl palmitate; astrocaryum murumuru seed butter; apple; milk thistle; acetyl hexapeptide-8; rice bran; pea; aminopropyl ascorbyl phosphate; .alpha.-tocopherol acetate; palmitoyl oligopeptide; caffeine; linoleic acid; cholesterol; acetylcarnitine hydrochloride; ascorbyl palmitate; ethylhexylglycerin; 7-dehydrocholesterol; tribehenin; zinc stearate; sorbitan isostearate; laureth-7; sucrose; propylene carbonate; caprylyl glycol; hyaluronate sodium; polyethylene glycol 400; hydrogenated soybean lecithin; xanthan gum; aluminum oxide; sodium chloride; butylated hydroxytoluene; chloroxylenol; phenoxyethanol; ferric oxide red; ferric oxide yellow; ferrosoferric oxide; mica

RE-NUTRIV ULTIMATE LIFTING CREME MAKEUP SPF15

Drug Facts

Active ingredient

Titanium Dioxide 1.40%

Purpose

Sunscreen

Use

helps prevent sunburn

Warnings

For external use only

Do not use on damaged or broken skin

When using this product keep out of eyes. Rinse with water to remove.

Stop use and ask a doctor if rash occurs

Keep out of reach of children. If product is swallowed, get medical help or contact a Poison Control Center right away.

Directions

For sunscreen use:

- apply liberally 15 minutes before sun exposure
- reapply at least every two hours
- use a water resistant sunscreen if swimming or sweating
- Sun Protection Measures. Spending time in the sun increases your risk of skin cancer and early skin aging. To decrease this risk, regularly use a sunscreen with a Broad Spectrum SPF value of 15 or higher and other sun protection measures including:
  - limit time in the sun, especially from 10 a.m. – 2 p.m.
  - wear long-sleeved shirts, pants, hats and sunglasses
- children under 6 months of age: ask a doctor

Inactive ingredients

water\aqua\eau • cyclopentasiloxane • butylene glycol • phenyl trimethicone • cetyl dimethicone • dimethicone • pentaerythrityl tetraethylhexanoate • octyldodecyl stearoyl stearate • peg/ppg-18/18 dimethicone • cetyl peg/ppg-10/1 dimethicone • magnesium sulfate • ethylhexyl palmitate • astrocaryum murumuru butter • pyrus malus (apple) fruit extract • silybum marianum (lady's thistle) extract • acetyl hexapeptide-8 • oryza sativa (rice) bran extract • pisum sativum (pea) extract • aminopropyl ascorbyl phosphate • tocopheryl acetate • palmitoyl oligopeptide • caffeine • linoleic acid • cholesterol • quaternium-90 bentonite • acetyl carnitine hcl • ascorbyl palmitate • disodium nadh • ethylhexylglycerin • 7-dehydrocholesterol • trimethylsiloxysilicate • tribehenin • phytosteryl/octyldodecyl lauroyl glutamate • methicone • zinc stearate • sorbitan isostearate • laureth-7 • sucrose • trifluoromethyl c1-4 alkyl dimethicone • glyceryl polymethacrylate • hydrolyzed fish (pisces) collagen • propylene carbonate • caprylyl glycol • sodium hyaluronate • peg-8 • hydrogenated lecithin • xanthan gum • alumina • fragrance (parfum) • sodium chloride • bht • chloroxylenol • phenoxyethanol • [+/- iron oxides (ci 77491, ci 77492, ci 77499) • titanium dioxide (ci 77891) • mica] <iln37196>

Other information

protect the product in this container from excessive heat and direct sun

PRINCIPAL DISPLAY PANEL - 30 ml Container Carton

ESTĒE LAUDER
Re-Nutriv

Ultimate Lifting Creme Makeup
Broad Spectrum SPF 15